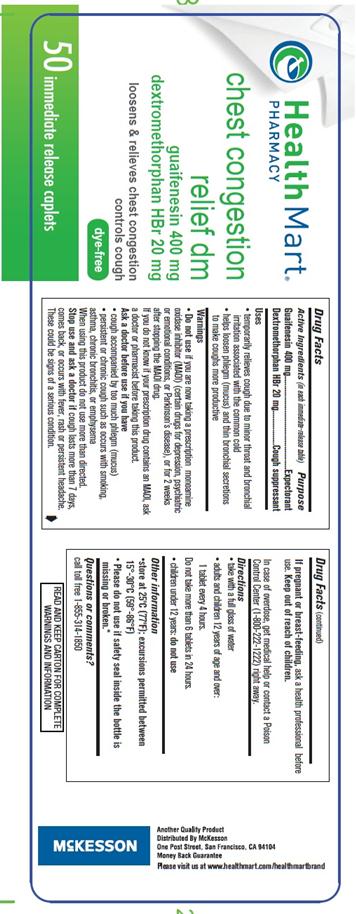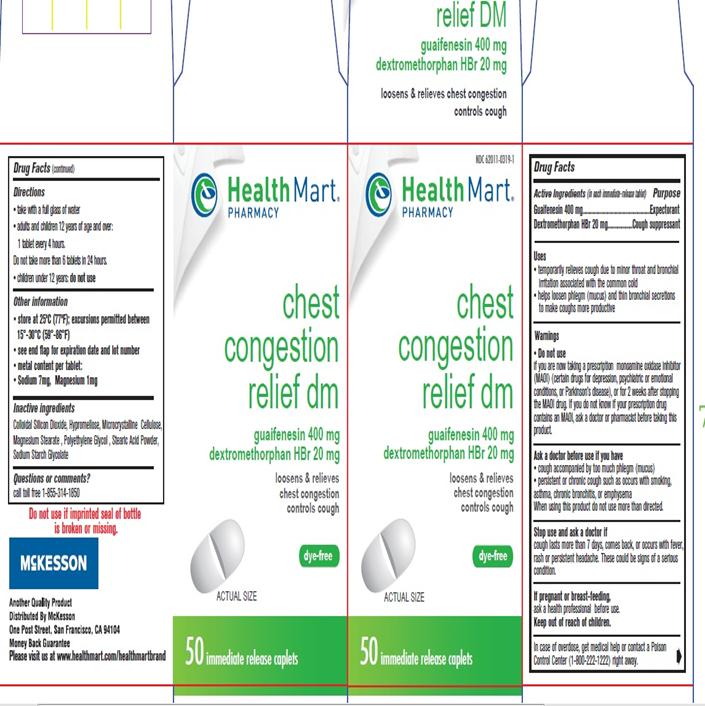 DRUG LABEL: Chest Congestion Relief
NDC: 62011-0319 | Form: TABLET
Manufacturer: Mckesson
Category: otc | Type: HUMAN OTC DRUG LABEL
Date: 20161218

ACTIVE INGREDIENTS: GUAIFENESIN 400 mg/1 1; DEXTROMETHORPHAN HYDROBROMIDE 20 mg/1 1
INACTIVE INGREDIENTS: SILICON DIOXIDE; HYPROMELLOSES; CELLULOSE, MICROCRYSTALLINE; MAGNESIUM STEARATE; POLYETHYLENE GLYCOLS; STEARIC ACID; SODIUM STARCH GLYCOLATE TYPE A CORN

Guaifenesin 400 mg

Active Ingredient

(in each intermediate release tablet)

Guaifenesin 400 mg

Dextromethorphan HBr 20 mg

Purpose

Expectorant

Cough Suppressant

Uses

- temporarily relieves cough due to minor throat and bronchial irritation associated with the common cold
- helps loosen phelgm (mucus) and thin bronchial secretions to make coughs more productive

Warnings

Do not use

If you are now taking a prescription monoamine oxidase inhibitor (MAOI) (certain drugs for depression, psychiatric or emotional conditions or parkinson’s disease) or for 2 weeks after stopping the MAOI drug. If you do not know your prescription drug contains an MAOI ask a doctor or pharmacist before taking this product.

Ask a doctor before use if you have

- cough accompanied by too much of phelgm (mucus)
- persistent or chronic cough such as occurs with smoking, asthma, chronic bronchitis, or emphysema
- when using this product do not use more than directed

Stop use and ask doctor if

Cough lasts more than 7 days, comes back, or occurs with fever, rash or persistent headache, these could be signs of a serious condition.

If pregnant or breast-feeding, ask a health professional before use.

Keep out of reach of children.

In case of overdose, get medical help or contact a Poison Control Center right away. (1-800-222-1222)

Directions

- take with full glass of water;
  1 tablet every 4 hours
- do not take more than 6 tablets in 24 hours
- children under 12 years: do not use

Other Information

- store at 25° C(77°F) ; excursion permitted between 15°-30° C (59°-86°F)
- see end flap for expiration date and lot number
- metal content per tablet:
- sodium 7mg, Magnesium 1mg

Inactive Ingredients

Colloidal Silicon Dioxide, Hypromellose, Microcrystalline cellulose, Magnesium stearate, Polyethylene Glycol, Stearic Acid powder, Sodium Starch Glycolate

Questions or Comments

Call 1-855-314-1850

PACKAGE LABEL.PRINCIPAL DISPLAY PANEL

NDC 62011-0319-1